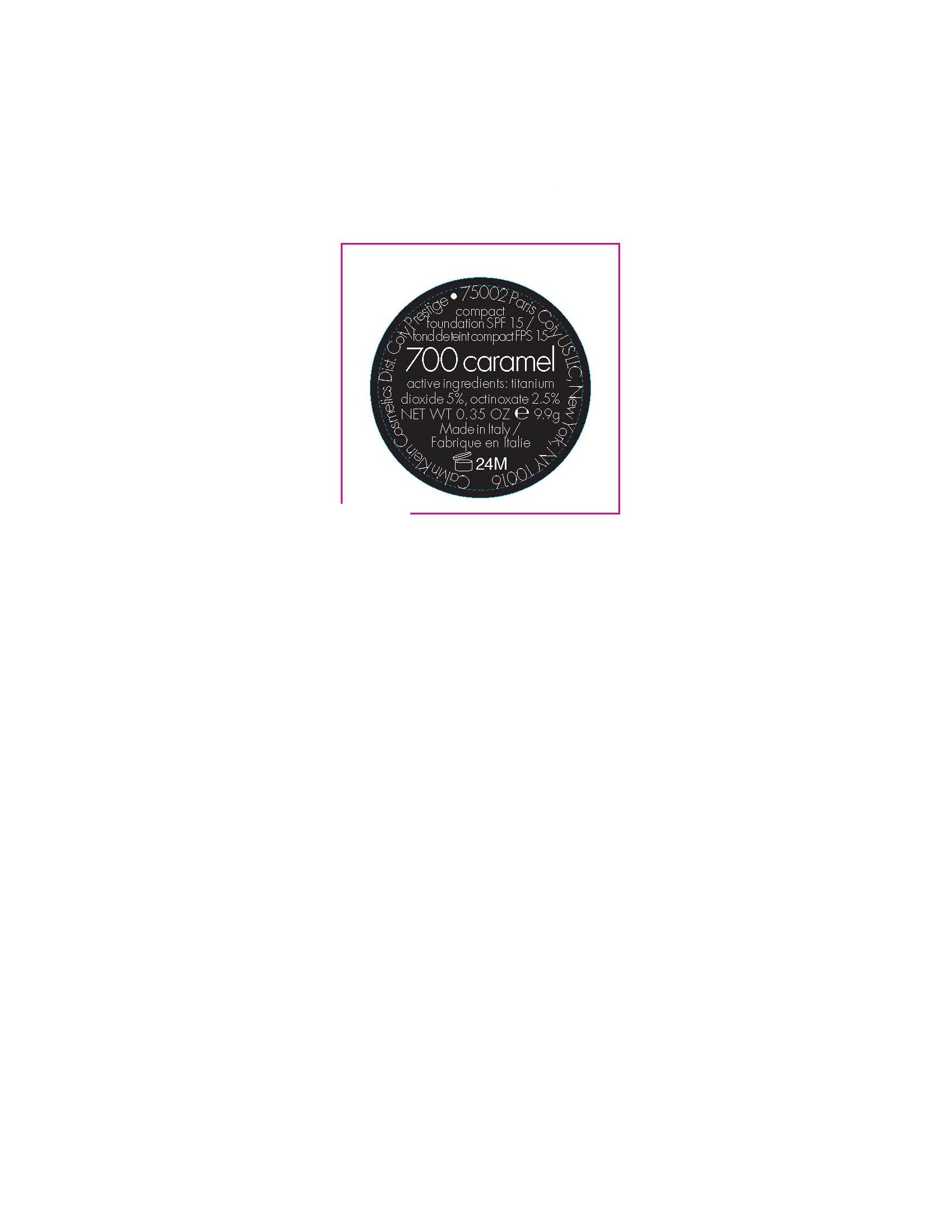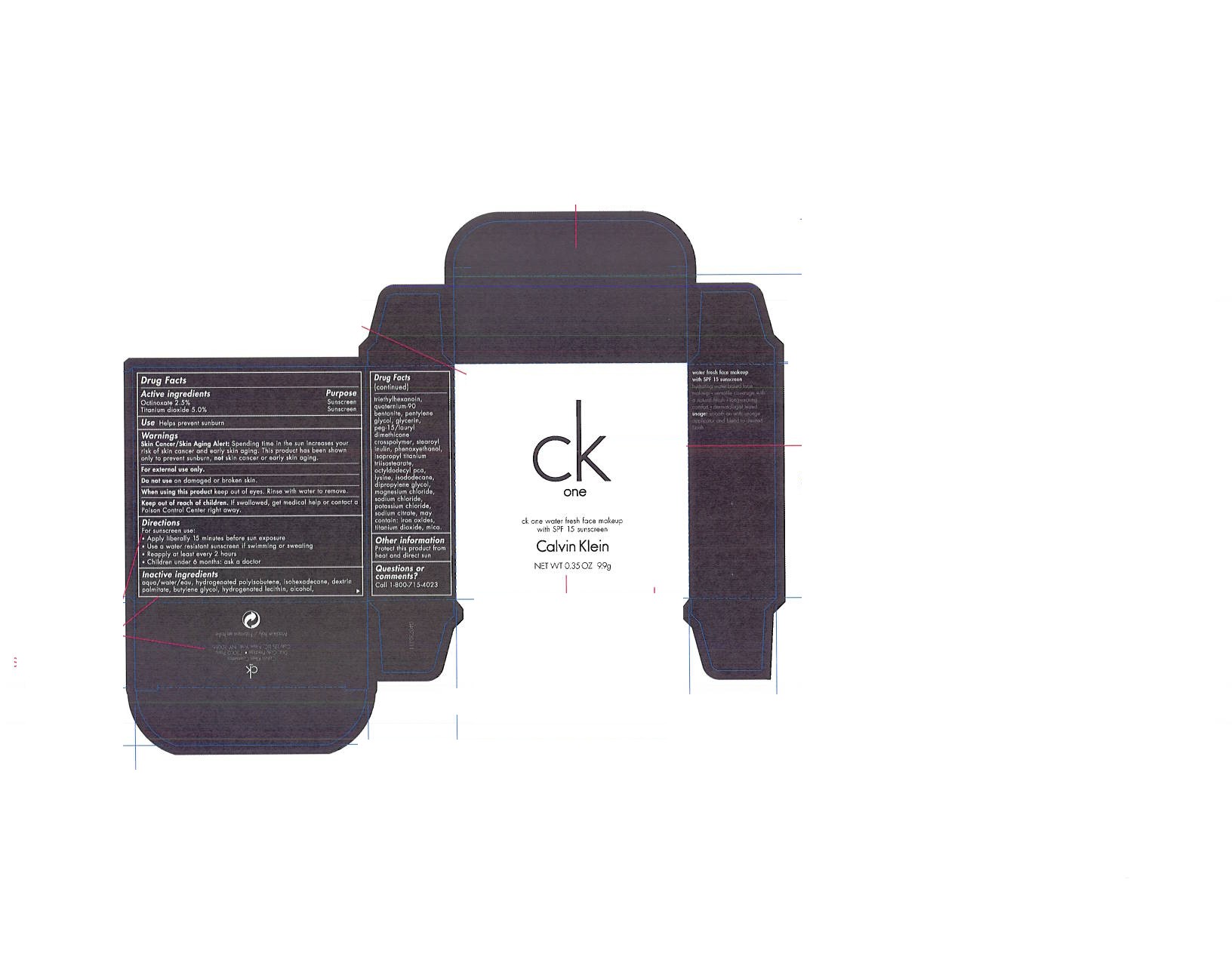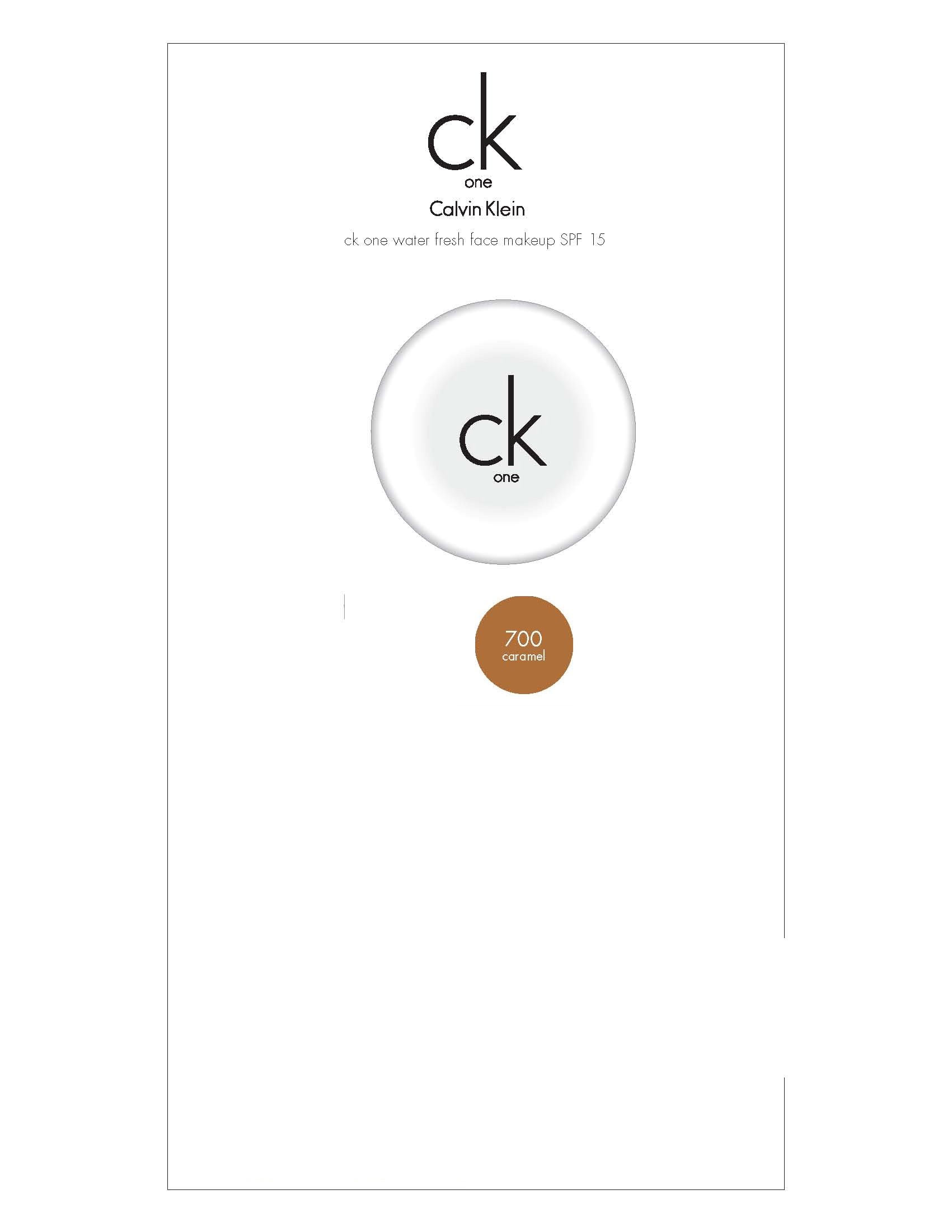 DRUG LABEL: ck one waterfresh face makeup spf 15 
NDC: 66184-480 | Form: CREAM
Manufacturer: Coty US LLC
Category: otc | Type: HUMAN OTC DRUG LABEL
Date: 20120123

ACTIVE INGREDIENTS: Titanium Dioxide 4.95 mL/9.9 g; Octinoxate 2.4 mL/9.9 g
INACTIVE INGREDIENTS: Water; Isohexadecane; Butylene Glycol ; Hydrogenated Soybean Lecithin  ; Alcohol ; Triethylhexanoin ; Pentylene Glycol ; Glycerin ; Lysine ; Isododecane ; Dipropylene Glycol ; Magnesium Chloride ; Sodium Chloride ; Potassium Chloride ; Sodium Citrate ; Mica 

Drug Facts

ACTIVE INGREDIENT

Octinoxate 2.5%

Titanium dioxide 5.0%

PURPOSE

Sunscreen

KEEP OUT OF REACH OF CHILDREN

Keep out of reach children. If swallowed, get medical help or contact a Poison Control Center right away.

INDICATIONS AND USAGE

Helps prevent sunburn

WARNINGS

Skin cancer/Skin Aging Alert: Spending time int he sun increases your risk of skin cancer and early skin aging. This product has been shown only to prevent sunburn, not skin cancer or early skin aging.

For external use only.
Do not use on damaged or broken skin.
When using this product keep out of eyes. Rinse with water to remove.

DOSAGE AND ADMINISTRATION

For sunscreen use:

- Apply liberally 15 minutes before sun exposure
- Use a water resistant sunscreen if swimming or sweating
- Reapply at least every 2 hours
- Children under 6 months: ask a doctor

INACTIVE INGREDIENT

aqua/water/eau, hydogentated polyisobutene, isohexadecane, dextrin palmitate, butylene glycol, hydrogenated lecithin, alcohol, triethylhexanoin, quaternium-90, bentonite, pentylene glycol, glycerin, peg-15/lauryl dimethicone crosspolymer, stearoyl inulin, phenoxyethanol, isopropl titanium triisostearate, octyldodectl pca, lysine, isododecane, dipropylene glycol, magnesium chloride, sodium chloride, sodium citrate, may contain: iron oxides, titanium dioxide, mica.